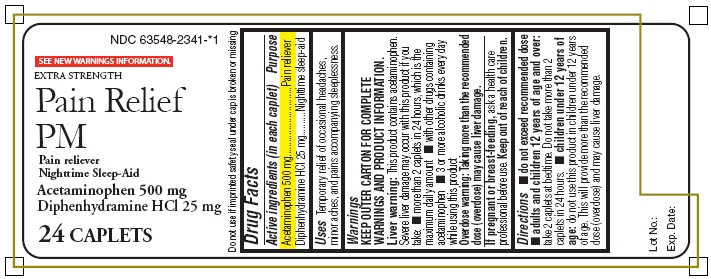 DRUG LABEL: Pain Relief PM
NDC: 63548-2341 | Form: TABLET, COATED
Manufacturer: Avema Pharma Solutions
Category: otc | Type: HUMAN OTC DRUG LABEL
Date: 20100205

ACTIVE INGREDIENTS: ACETAMINOPHEN 500 mg/1 1; DIPHENHYDRAMINE HYDROCHLORIDE 25 mg/1 1
INACTIVE INGREDIENTS: FD&C BLUE NO. 1; MAGNESIUM STEARATE; CELLULOSE, MICROCRYSTALLINE; POLYETHYLENE GLYCOL 400; POLYVINYL ALCOHOL; POVIDONE K30; CARBOXYMETHYLCELLULOSE SODIUM; STARCH, CORN; STEARIC ACID; TALC; TITANIUM DIOXIDE

Drug Facts

Active ingredients (in each caplet)

Acetaminophen 500 mg*

Diphenhydramine HCl 25 mg**

Purpose

*Pain reliever

**Nighttime sleep aid

Uses

Temporary relief of occasional headaches, minor aches, and pains accompanying sleeplessness.

Warnings

Liver warning: This product contains acetaminophen. Severe liver damage may occur with this product if you take:

- more than 2 caplets in 24 hours, which is the maximum daily amount
- with other drugs containing acetaminophen
- 3 or more alcoholic drinks every day while using this product

Overdose warning: Taking more than the recommended dose (overdose) may cause liver damage. In case of overdose, get medical help or contact a Poison Control Center right away. Prompt medical attention is critical for adults as well as children even if you do not notice any signs or symptoms.

Do not use

- with other products containing acetaminophen (prescription or nonprescription). If you are not sure whether a drug contains acetaminophen, ask a doctor or pharmacist.
- in children under 12 years of age
- with other products containing diphenhydramine, even one used on skin

Ask a doctor before use if you have

- liver disease
- asthma
- breathing problems such as emphysema or chronic bronchitis
- glaucoma
- difficulty in urinating due to an enlargement of the prostate gland

Ask a doctor or pharmacist before use if you are

- taking sedatives or tranquilizers
- taking the blood thinning drug warfarin

When using this product

avoid alcoholic beverages

do not drive a motor vehicle or operate machinery. This product will cause drowsiness.

Stop use and ask a doctor if

- sleeplessness persists continuously for more than 2 weeks. Insomnia may be a symptom of a serious underlying medical illness.
- pain gets worse or lasts for more than 10 days
- fever gets worse or lasts for more than 3 days
- new symptoms occur
- redness or swelling is present

PREGNANCY OR BREAST FEEDING

If pregnant or breast-feeding, ask a health care professional before use. Keep out of reach of children.

Directions

- do not exceed recommended dose
- adults and children 12 years of age and over: take 2 caplets at bedtime. Do not take more than 2 caplets in 24 hours.
- children under 12 years of age: do not use this product in children under 12 years of age. This will provide more than the recommended dose (overdose) and may cause liver damage.

Other information

- store at room temperature 15°-30°C (59°-86°F), avoid high humidity and excessive heat
- do not use if imprinted safety seal under cap is broken or missing

Inactive ingredients

FD&C Blue #1 Aluminum Lake, magnesium stearate, microcrystalline cellulose, polyethylene glycol (PEG), polyvinyl alcohol, polyvinylpyrrolidone, sodium carboxymethyl starch, starch, stearic acid, talc, titanium dioxide.

Package/Label Principal Display Panel

NDC 63548-2341-*1

SEE NEW WARNINGS INFORMATION

EXTRA STRENGTH

Pain Relief PM

Pain reliever

Nighttime Sleep-Aid

Acetaminophen 500 mg

Diphenhydramine HCl 25 mg

24 CAPLETS

Do not use if imprinted safety seal under cap is broken or missing